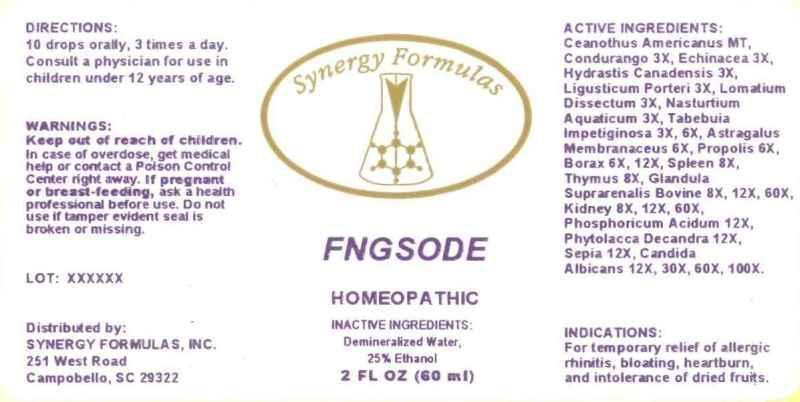 DRUG LABEL: FNGSODE
NDC: 43772-0016 | Form: LIQUID
Manufacturer: Synergy Formulas, Inc.
Category: homeopathic | Type: HUMAN OTC DRUG LABEL
Date: 20130812

ACTIVE INGREDIENTS: CEANOTHUS AMERICANUS LEAF 1 [hp_X]/1 mL; MARSDENIA CONDURANGO BARK 3 [hp_X]/1 mL; ECHINACEA, UNSPECIFIED 3 [hp_X]/1 mL; GOLDENSEAL 3 [hp_X]/1 mL; LIGUSTICUM PORTERI ROOT 3 [hp_X]/1 mL; LOMATIUM DISSECTUM ROOT 3 [hp_X]/1 mL; NASTURTIUM OFFICINALE 3 [hp_X]/1 mL; TABEBUIA IMPETIGINOSA BARK 3 [hp_X]/1 mL; ASTRAGALUS PROPINQUUS ROOT 6 [hp_X]/1 mL; PROPOLIS WAX 6 [hp_X]/1 mL; SODIUM BORATE 6 [hp_X]/1 mL; BOS TAURUS SPLEEN 8 [hp_X]/1 mL; BOS TAURUS THYMUS 8 [hp_X]/1 mL; BOS TAURUS ADRENAL GLAND 8 [hp_X]/1 mL; PORK KIDNEY 8 [hp_X]/1 mL; PHOSPHORIC ACID 12 [hp_X]/1 mL; PHYTOLACCA AMERICANA ROOT 12 [hp_X]/1 mL; SEPIA OFFICINALIS JUICE 12 [hp_X]/1 mL; CANDIDA ALBICANS 12 [hp_X]/1 mL
INACTIVE INGREDIENTS: WATER; ALCOHOL

DRUG FACTS:

ACTIVE INGREDIENTS:

Ceanothus Americanus 1X, Condurango 3X, Echinacea 3X, Hydrastis Canadensis 3X, Ligusticum Porteri 3X, Lomatium Dissectum 3X, Nasturtium Aquaticum 3X, Tabebuia Impetiginosa 3X, 6X, Astragalus Membranaceus 6X, Propolis 6X, Borax 6X, 12X, Spleen (Bovine) 8X, Thymus (Bovine) 8X, Glandula Suprarenalis Bovine 8X, 12X, 60X, Kidney (Suis) 8X, 12X, 60X, Phosphoricum Acidum 12X, Phytolacca Decandra 12X, Sepia 12X, Candida Albicans 12X, 30X, 60X, 100X.

INDICATIONS:

For temporary relief of allergic rhinitis, bloating, heartburn, and intolerance of dried fruits.

WARNINGS:

Keep out of reach of children. In case of overdose, get medical help or contact a Poison Control Center right away.

If pregnant or breast-feeding, as a health professional before use.

Do not use if tamper evident seal is broken or missing.

DIRECTIONS:

10 drops orally, 3 times a day. Consult a physician for use in children under 12 years of age.

INACTIVE INGREDIENTS:

Demineralized Water, 25% Ethanol

Keep out of reach of children. In case of overdose, get medical help or contact a Poison Control Center right away.

INDICATIONS:

For temporary relief of allergice rhinitis, bloating, heartburn, and intolerance of dried fruits.

QUESTIONS:

Distributed by:

SYNERGY FORMULAS, INC.

251 West Road

Campobello, SC 29322

PACKAGE DISPLAY LABEL:

Synergy Formulas

FNGSODE

HOMEOPATHIC

2 FL OZ (60 mL)